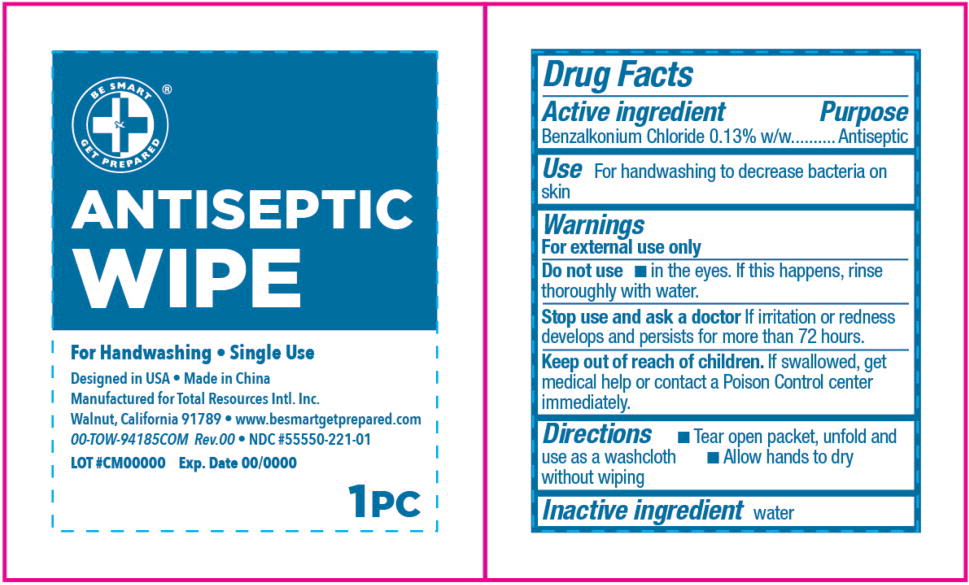 DRUG LABEL: ANTISEPTIC WIPE
NDC: 55550-221 | Form: PATCH
Manufacturer: Total Resources International Inc.
Category: otc | Type: HUMAN OTC DRUG LABEL
Date: 20251010

ACTIVE INGREDIENTS: BENZALKONIUM CHLORIDE
 0.13 g/100 g
INACTIVE INGREDIENTS: WATER

Drug Facts

Active ingredient

Benzalkonium Chloride 0.13% w/w.

Purpose

Antiseptic

Use

For handwashing to decrease bacteria on skin

Warnings

For external use only

Do not use

- in the eyes. If this happens, rinse thoroughly with water.

Stop use and ask a doctor If irritation or redness develops and persists for more than 72 hours.

Keep out of reach of children. If swallowed, get medical help or contact a Poison Control center immediately.

Directions

- Tear open packet, unfold and use as a washcloth
- Allow hands to dry without wiping

Inactive ingredient

water